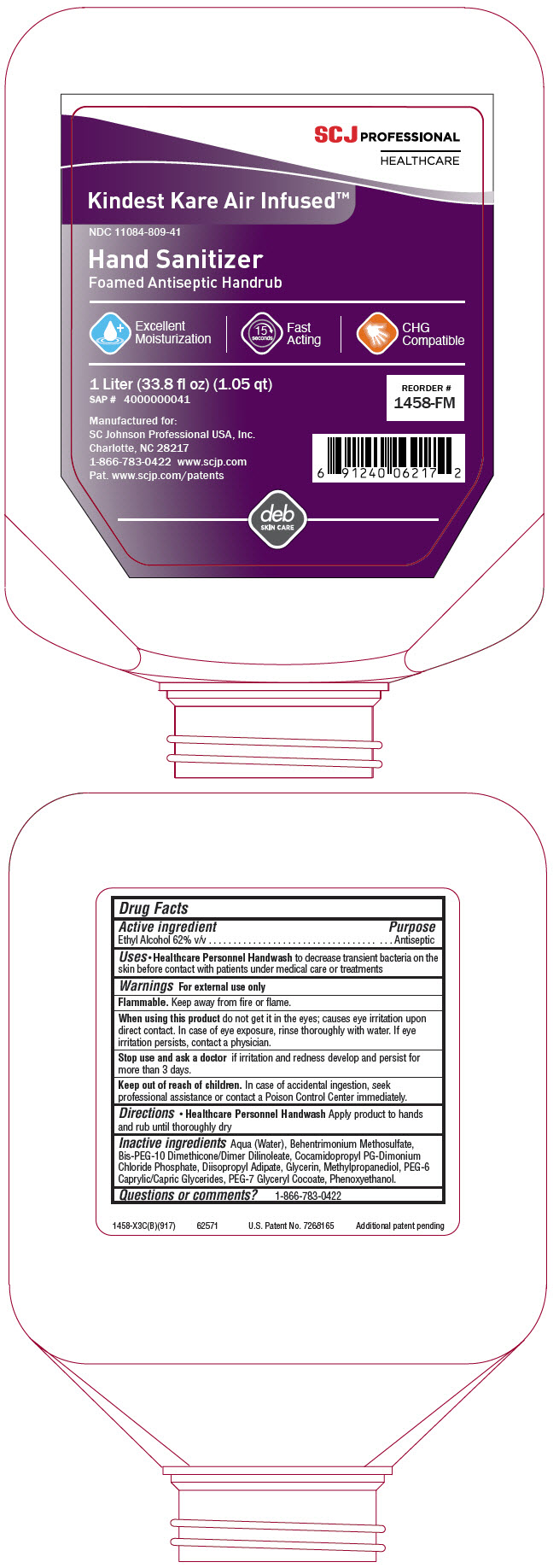 DRUG LABEL: Kindest Kare Air-Infused Foam Antiseptic Handrub
NDC: 11084-809 | Form: LIQUID
Manufacturer: SC Johnson Professional USA, Inc.
Category: otc | Type: HUMAN OTC DRUG LABEL
Date: 20201221

ACTIVE INGREDIENTS: ALCOHOL 62 mg/100 mL
INACTIVE INGREDIENTS: water; Bis-PEG-10 Dimethicone/Dimer Dilinoleate Copolymer; methylpropanediol; phenoxyethanol; behentrimonium methosulfate; PEG-7 glyceryl cocoate; glycerin; CAPRYLOCAPROYL POLYOXYLGLYCERIDES 6; DIISOPROPYL ADIPATE; COCAMIDOPROPYL PROPYLENE GLYCOL-DIMONIUM CHLORIDE PHOSPHATE

Kindest Kare Air-Infused™ Foam Antiseptic Handrub

Drug Facts

Active ingredient

Ethyl Alcohol 62% v/v

Purpose

Antiseptic

Uses

- Healthcare Personnel Handwash to decrease transient bacteria on the skin before contact with patients under medical care or treatments

Warnings

For external use only

Flammable. Keep away from fire or flame.

When using this product do not get it in the eyes; causes eye irritation upon direct contact. In case of eye exposure, rinse thoroughly with water. If eye irritation persists, contact a physician.

Stop use and ask a doctor if irritation and redness develop and persist for more than 3 days.

Keep out of reach of children. In case of accidental ingestion, seek professional assistance or contact a Poison Control Center immediately.

Directions

- Healthcare Personnel Handwash Apply product to hands and rub until thoroughly dry

Inactive ingredients

Aqua (Water), Behentrimonium Methosulfate, Bis-PEG-10 Dimethicone/Dimer Dilinoleate, Cocamidopropyl PG-Dimonium Chloride Phosphate, Diisopropyl Adipate, Glycerin, Methylpropanediol, PEG-6 Caprylic/Capric Glycerides, PEG-7 Glyceryl Cocoate, Phenoxyethanol.

Questions or comments?

1-866-783-0422

PRINCIPAL DISPLAY PANEL - 1 Liter Bottle Label

SCJ PROFESSIONAL
HEALTHCARE

Kindest Kare Air Infused™

NDC 11084-809-41

Hand Sanitizer
Foamed Antiseptic Handrub

Excellent
Moisturization

15
seconds
Fast
Acting

CHG
Compatible

1 Liter (33.8 fl oz) (1.05 qt)
SAP # 4000000041

REORDER #
1458-FM

Manufactured for:
SC Johnson Professional USA, Inc.
Charlotte, NC 28217
1-866-783-0422 www.scjp.com
Pat. www.scjp.com/patents

deb
SKIN CARE